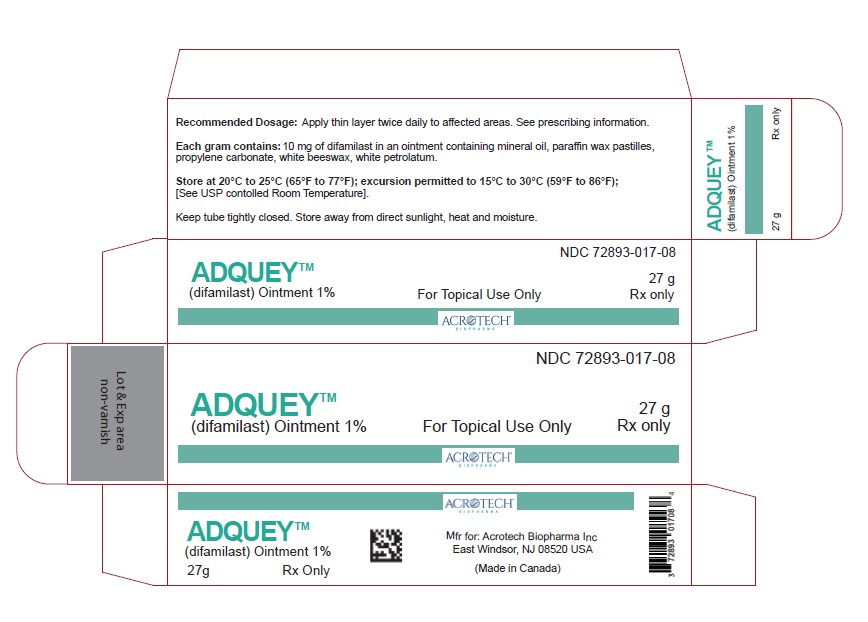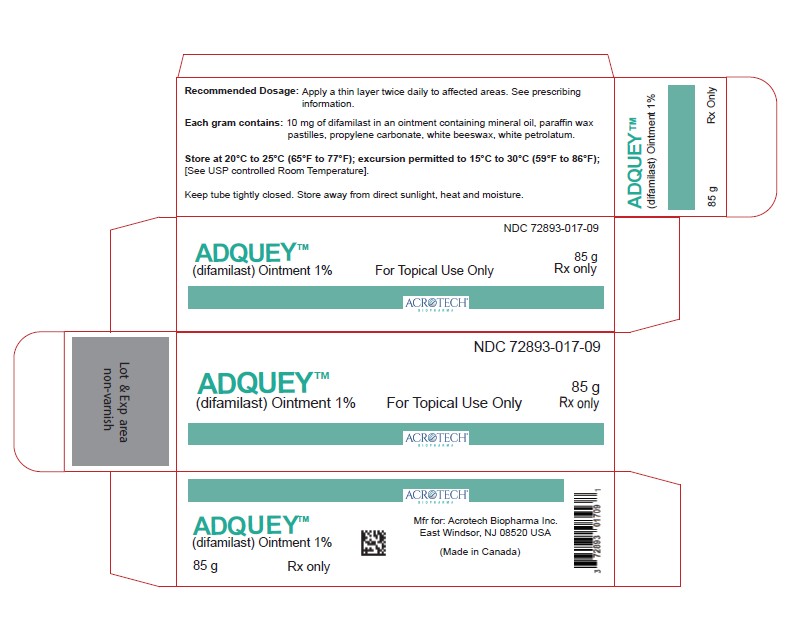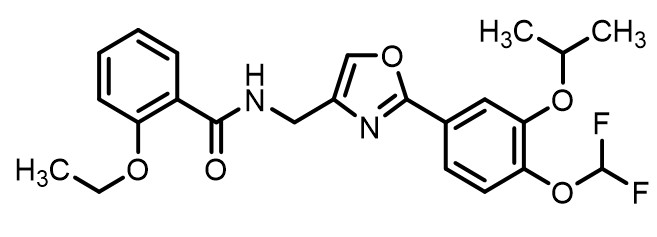 DRUG LABEL: Difamilast
NDC: 72893-017 | Form: OINTMENT
Manufacturer: Acrotech Biopharma Inc
Category: prescription | Type: Human Prescription Drug Label
Date: 20260225

ACTIVE INGREDIENTS: Difamilast 10 mg/100 g
INACTIVE INGREDIENTS: MINERAL OIL; PARAFFIN; PROPYLENE CARBONATE; WHITE PETROLATUM; WHITE WAX

HIGHLIGHTS OF PRESCRIBING INFORMATION

These highlights do not include all the information needed to use ADQUEY safely and effectively. See full prescribing information for ADQUEY.
ADQUEY™(difamilast) ointment, for topical use Initial U.S. Approval: 2026

1 INDICATIONS & USAGE

ADQUEY is a phosphodiesterase 4 inhibitor indicated for the topical treatment of adults and pediatric patients 2 years of age and older with mild to moderate atopic dermatitis. (1)

2 DOSAGE & ADMINISTRATION

- For topical use only. Not for ophthalmic, oral, or intravaginal use. (2)
- Apply a thin layer of ADQUEY twice daily to affected areas and rub in completely. (2)

3 DOSAGE FORMS & STRENGTHS

Ointment: 1%. (3)

4 CONTRAINDICATIONS

None. (4)

6 ADVERSE REACTIONS

The most common adverse reaction occurring in ≥1% of subjects is nasopharyngitis. (6.1)

To report SUSPECTED ADVERSE REACTIONS, contact Acrotech Biopharma Inc. at 1-888-292-9617 or FDA at 1-800-FDA-1088 or www.fda.gov/medwatch.

FULL PRESCRIBING INFORMATION

1 INDICATIONS & USAGE

ADQUEY is indicated for the topical treatment of adults and pediatric patients 2 years of age and older with mild to moderate atopic dermatitis.

2 DOSAGE & ADMINISTRATION

ADQUEY is for topical use only and not for ophthalmic, oral, or intravaginal use.
Apply a thin layer of ADQUEY twice daily to affected areas and rub in completely.
Wash hands after application.
Avoid areas of the skin that are infected when applying ADQUEY.

3 DOSAGE FORMS & STRENGTHS

Ointment: 1% (10 mg of difamilast per gram) of white to off-white ointment.

4 CONTRAINDICATIONS

None.

6 ADVERSE REACTIONS

6.1 Clinical Trial Experience

Because clinical trials are conducted under widely varying conditions, adverse reaction rates observed in the clinical trials of a drug cannot be directly compared to rates in the clinical trials of another drug and may not reflect the rates observed in practice.

The safety of ADQUEY was assessed in two double-blind, vehicle-controlled clinical trials (Trial 2 and Trial 3) that enrolled 532 adult and pediatric subjects 2 years of age and older in Japan with mild to moderate atopic dermatitis (AD). Subjects applied ADQUEY or vehicle ointment topically twice daily for 4 weeks [see Clinical Studies (14)]. Adverse reactions reported by ≥1% of ADQUEY-treated subjects and more frequently than in subjects receiving vehicle are listed in Table 1.

Table 1: Adverse Reactions Occurring in ≥1% of Adult and Pediatric Subjects 2 Years of Age and Older Treated with ADQUEY for Mild to Moderate Atopic Dermatitis (and Greater than Vehicle) through Week 4 in Trials 2 and 3

Adverse Reaction | ADQUEY (N=267) n (%) | Vehicle (N=265) n (%)
Nasopharyngitis | 16(6) | 10(4)

Less common (<1%) adverse reactions in subjects treated with ADQUEY in Trials 2 and 3 included application site folliculitis, contact dermatitis, application site rash, and molluscum contagiosum.

In Trial 1, a vehicle-controlled dose ranging trial, 43 subjects 10 years of age and older in the United States, Australia, and Poland received ADQUEY topically twice daily for 8 weeks and the safety profile was consistent with Trials 2 and 3.
In two additional vehicle-controlled dose ranging trials (Trial 4 and Trial 5), 92 subjects 2 years of age and older in Japan received ADQUEY topically twice daily for 4 weeks (Trial 4) and twice daily for 8 weeks (Trial 5) and the safety profile was consistent with Trials 2 and 3.
In open-label trials of both Japanese and United States (US) subjects, 857 adult and pediatric subjects continued twice-daily treatment with ADQUEY for up to 52 weeks. The following application site adverse reactions occurred that led to drug discontinuation: pain, pruritus, vesicles, blistering, erythema, burning and contact dermatitis.

6.2 Postmarketing Experience

The following adverse reactions have been identified during post approval use of ADQUEY. Because these reactions are reported voluntarily from a population of uncertain size, it is not always possible to reliably estimate their frequency or establish a causal relationship to drug exposure.
General disorders and administration site condition: application site swelling.

8 USE IN SPECIFIC POPULATIONS

8.1 Pregnancy

Risk Summary
The available data on the use of topical difamilast during pregnancy are insufficient to evaluate for a drug-associated risk of major birth defects, miscarriage, or other adverse maternal or fetal outcomes.

In animal reproduction studies, difamilast administered subcutaneously to pregnant rats and rabbits during the period of organogenesis produced no fetal structural abnormalities at doses up to 30 and 3 times the maximum recommended human dose (MRHD), respectively. Difamilast induced increased post-implantation loss, decreased fetal weight, retarded ossification and increased visceral abnormalities in rats at subcutaneous dose 263 times the MRHD. Difamilast induced increased skeletal variations in rabbits at subcutaneous doses 14 times the MRHD (see Data). The background risk of major birth defects and miscarriage for the indicated population is unknown. All pregnancies have a background risk of birth defects, loss, and other adverse outcomes. In the U.S. general population, the estimated background risk of major birth defects and miscarriage in clinically recognized pregnancies is 2% to 4% and 15% to 20%, respectively.

Data
Animal Data
In an embryo-fetal development study, pregnant rats were dosed subcutaneously during the period of organogenesis with up to 100 mg/kg/day difamilast (263 times the MRHD based on AUC comparison). Increased post-implantation loss, decreased fetal weight, retarded ossification, and increased visceral abnormalities (membranous ventricular septum defect) were noted at 100 mg/kg/day (263 times the MRHD based on AUC comparison). No embryo-fetal toxicity was observed at 10 mg/kg/day (30 times the MRHD based on AUC comparison).

In an embryo-fetal development study in rabbits, pregnant does were dosed subcutaneously during the period of organogenesis with up to 3 mg/kg/day difamilast (14 times the MRHD based on AUC comparison). Increased skeletal variations (increased supernumerary lumbar vertebra) were observed at 3 mg/kg/day (14 times the MRHD based on AUC comparison). No embryo-fetal toxicity was observed at 1 mg/kg/day (3 times the MRHD based on AUC comparison).
In a pre- and post-natal development study in rats, dams were dosed subcutaneously with up to 3 mg/kg/day difamilast during the periods of organogenesis and lactation. No treatment-related adverse effects on reproductive functions of dams, or pre- and post-natal development of offspring were observed at 3 mg/kg/day (13 times the MRHD based on AUC comparison).

8.2 Lactation

Risk Summary
There are no data on the presence of difamilast or its metabolites in human milk, the effects on the breastfed infant, or the effects on milk production.
Difamilast and/or its metabolites are excreted into the milk of lactating rats (see Data). When a drug is present in animal milk, it is likely that the drug will be present in human milk. The developmental and health benefits of breastfeeding should be considered along with the mother’s clinical need for ADQUEY and any potential adverse effects on the breastfed infant from ADQUEY or from the underlying maternal condition.

Clinical Considerations
To minimize potential infant exposure, advise breastfeeding women not to apply ADQUEY directly to the nipple or areola. If applied to the patient's chest, avoid exposure via direct contact with the infant's skin.
Data
When ^14C-difamilast was subcutaneously administered to lactating rats at a single dose of 3 mg/kg, the concentration of radioactivity in milk was higher than that in blood (with milk/blood ratios at Cmax and AUC∞ of 13.7 and 5.4, respectively). The concentration of difamilast in animal milk does not necessarily predict the concentration of drug in human milk.

8.4 Pediatric Use

The safety and effectiveness of ADQUEY for the topical treatment of mild to moderate atopic dermatitis have been established in pediatric patients 2 years of age and older. Use of ADQUEY in this age group is supported by data from five vehicle-controlled trials, which included 236 subjects 2 to less than 17 years of age, of whom 119 received ADQUEY and 117 received vehicle [see Adverse Reactions (6.1), Clinical Pharmacology (12.3) and Clinical Studies (14)].
The safety and effectiveness of ADQUEY have not been established in pediatric patients younger than 2 years of age.

8.5 Geriatric Use

In clinical trials of ADQUEY in subjects with mild to moderate atopic dermatitis, 2 subjects were 65 years of age or older, and 0 were aged 75 years and older. Clinical trials of ADQUEY did not include sufficient numbers of subjects aged 65 and over to determine whether they respond differently from younger adult subjects.

11 DESCRIPTION

ADQUEY (difamilast) ointment contains difamilast as the active ingredient. Difamilast, is a phosphodiesterase-4 (PDE-4) inhibitor.
Difamilast is described chemically as N-({2-[4-(Difluoromethoxy)-3-(propan-2-yloxy)phenyl]-1,3-oxazol-4-yl}methyl)-2-ethoxybenzamide. The empirical formula is C23H24F2N2O5 and the molecular weight is 446.44 g/mol.
The structural formula is represented below:

Difamilast occurs as white (or practically white) crystals or crystalline powder. It is very soluble in N-methylpyrrolidone, freely soluble in methanol and ethanol (99.5), and practically insoluble in water. It shows crystal polymorphism.
Each gram of ADQUEY contains 1% difamilast (w/w) in a wax-based, white to off-white ointment containing the following inactive ingredients: mineral oil, paraffin, propylene carbonate, white petrolatum, and white wax.

12 CLINICAL PHARMACOLOGY

12.1 Mechanism of Action

Difamilast is an inhibitor of phosphodiesterase-4 (PDE-4). Difamilast’s inhibition of PDE-4 (a major cyclic adenosine monophosphate (AMP)-metabolizing enzyme) activity leads to accumulation of intracellular cyclic AMP and decreased productions of various cytokines and chemokines. However, the specific mechanism(s) by which difamilast exerts its therapeutic action is not well defined.

12.2 Pharmacodynamics

The pharmacodynamics of ADQUEY ointment in the treatment of atopic dermatitis is not known.
Cardiac Electrophysiology
ADQUEY ointment is not expected to cause clinically significant QTc interval prolongation at the recommended dosages.

12.3 Pharmacokinetics

Absorption
The pharmacokinetics (PK) of ADQUEY were investigated in 31 pediatric subjects 2 years of age and older with moderate to severe atopic dermatitis and a mean ± SD body surface area (BSA) involvement of 44 ± 13% (range 25% to 80%). In this trial, subjects applied an average of approximately 4.3 g of ADQUEY ointment, 1% (dose range was 1.7 to 11.7 g per application) twice daily for 2 weeks.
Plasma concentrations were quantifiable in all the subjects. On Day 15, the mean ± SD maximum plasma concentration (Cmax) and area under the concentration time curve from 0 to 8 hours post dose (AUC0-8) for difamilast were 16.9 ± 21.9 ng/mL and 86.2 ± 79.6 ng*h/mL, respectively. Systemic concentrations of difamilast were at steady state by Day 15, with no evidence of accumulation.
The PK of ADQUEY were investigated in 31 adult subjects with mild to moderate atopic dermatitis and a mean ± SD BSA involvement of 6 ± 3% (range 3% to 19%). Subjects applied an average of approximately 0.9 g of ADQUEY ointment, 1% (dose range was 0.1 to 3.8 g per application) twice daily for 4 weeks. On Day 29, the mean ± SD Cmax and AUC0-12 for difamilast were 0.76 ± 1.16 ng/mL and 6.10 ± 8.85 ng*h/mL, respectively.

Distribution
Difamilast serum protein binding is 99% and is not concentration-dependent, in vitro.

Elimination
Metabolism
Difamilast is substantially metabolized to form three major metabolites in the plasma via CYP3A4-mediated O-deethylation (Metabolite 1), CYP1A2-mediated hydroxylation (Metabolite 2), and enzymatic hydrolysis (Metabolite 3).

Excretion
After both single dosing and twice daily administration of difamilast ointment 1% in healthy Japanese subjects for 2 weeks, difamilast and Metabolite 1 were undetectable in urine. The urinary excretion ratios of all the other metabolites were less than 0.1% of the administered dose.

Specific Populations
No dedicated clinical trials have been conducted to assess the impact of intrinsic factors on the PK of difamilast. Based on cross-study analyses, no substantial differences in the PK of difamilast were observed based on age (2-70 years), sex, race, mild or moderate renal impairment, or mild or moderate hepatic impairment. The effect of severe renal impairment (eGFR < 30 mL/min), or severe (Child-Pugh Class C) hepatic impairment on difamilast PK is unknown.

Pediatric Patients
The plasma difamilast trough concentration corrected by dose in pediatric patients was 1.3 to 1.9 times higher than that in adults (on Day 1 and Day 15, respectively).
Drug Interaction Studies
Clinical Studies
No clinical drug interaction trials have been conducted with topical difamilast.

In Vitro Studies
CYP450 Enzymes: Difamilast is a substrate of CYP3A4 and CYP1A2. Difamilast is not expected to inhibit CYP1A2, CYP2A6, CYP2B6, CYP2C8, CYP2C9, CYP2C19, CYP2D6, CYP2E1, and CYP3A4 at clinically relevant concentrations. Induction of CYP1A2, CYP2B6, CYP2C9, and CYP3A4 by difamilast is expected to be low at clinically relevant concentrations.
Transporter Systems: Difamilast is a substrate of breast cancer resistance protein (BCRP),but is not a substrate of P-glycoprotein (P-gp), OATP1B1, or OATP1B3. Difamilast is not expected to inhibit P-gp, BCRP, OAT1, OAT3, OCT1, OCT2, OATP1B1, OATP1B3, MATE1, or MATE2-K at clinically relevant concentrations.

13 NONCLINICAL TOXICOLOGY

13.1 Carcinogenesis & Mutagenesis & Impairment Of Fertility

In a 2-year dermal carcinogenicity study in rats, no test article-related neoplastic findings were observed in male or female rats that received difamilast at dermal doses up to 3% ointment applied at 0.008 ml/cm^2 (4 times the MRHD based on AUC comparison).
In a 2-year dermal carcinogenicity study in mice, no test article-related neoplastic findings were observed in male or female mice that received difamilast at dermal doses up to 3% ointment applied at 0.008 ml/cm^2 (4 times the MRHD based on AUC comparison).
Difamilast was not genotoxic in an in vitro bacterial reverse mutation (Ames) test, an in vitro mammalian cell mutation test in mouse lymphoma cells, or an in vivo rat bone marrow micronucleus test.
In a fertility and early embryonic development study in rats, irregular estrus cycles, sperm abnormalities, increased preimplantation loss, and decreased copulation and fertility indexes were observed at a subcutaneous dose of 100 mg/kg/day difamilast (116 times the MRHD for males and 263 times the MRHD for females, respectively, based on AUC comparison). No treatment-related adverse effects on fertility or early embryonic development were observed at 10 mg/kg/day for males and females (20 times the MRHD for males and 30 times the MRHD for females, respectively, based on AUC comparison).

14 CLINICAL STUDIES

The efficacy of ADQUEY for the treatment of mild to moderate atopic dermatitis was assessed in three multicenter, randomized, double-blind, parallel-group, vehicle-controlled trials (Trial 1 [NCT02068352], Trial 2 [NCT03908970], and Trial 3 [NCT03911401]) that treated a total of 612 subjects. Trial 1 enrolled adult and pediatric subjects 10 years of age and older in the United States, Australia, and Poland. Trial 2 enrolled adult and pediatric subjects 15 years of age and older in Japan, and Trial 3 enrolled pediatric subjects 2 to 14 years of age in Japan. In these trials, subjects were randomized 1:1 to receive ADQUEY or vehicle ointment, applied topically to the entire treatment area twice daily for at least 4 weeks.
The trials enrolled subjects with an Investigator's Global Assessment (IGA) score of 2 (mild) or 3 (moderate) atopic dermatitis and affected body surface area (BSA) (excluding the face, neck, and head [Trial 1]; excluding the scalp [Trials 2 and 3]) of ≥ 5% and ≤ 40%. The IGA included an overall assessment of atopic dermatitis (erythema, induration/papulation, and oozing/crusting) on a severity scale of 0 to 4.
At baseline, 29%, 15%, and 15% of the subjects had an IGA of mild, and 71%, 85%, and 85% had an IGA of moderate in Trials 1, 2, and 3, respectively. Concomitant treatment for atopic dermatitis was prohibited.
In Trial 1, 56% of the subjects were female, 73% were White, 20% were Black or African American, and 4% were Asian; for ethnicity, 18% of the subjects identified as Hispanic or Latino. In Trials 2 and 3, the majority of the subjects were male (54% in Trial 2 and 58% in Trial 3), 100% were Asian, and 100% identified as Not Hispanic or Latino. The median age of enrolled subjects at baseline was 30 years (range 10 to 67 years), 30 years (range 15 to 65 years), and 7 years (range 2 to 14 years) in Trials 1, 2, and 3, respectively.
The primary efficacy endpoint for all trials was the proportion of subjects who achieved IGA success, defined as an IGA grade of clear (0) or almost clear (1) and with a 2-grade or greater improvement from baseline, at Week 4.
The efficacy results at Week 4 are shown in Table 2.
Table 2: Efficacy Results at Week 4 in Adult and Pediatric Subjects 2 Years of Age and Older with Mild to Moderate Atopic Dermatitis in Trials 1, 2, and 3

 | Trial 1 (Multinational‡) |  | Trial 2 (Japan) |  | Trial 3 (Japan)
 | ADQUEY (N = 43) | Vehicle (N = 37) | ADQUEY (N = 182) | Vehicle (N = 182) | ADQUEY (N = 85) | Vehicle (N = 83)
IGA Success†, n (%) | 9 (21) | 1 (3) | 70 (38) | 23 (13) | 40 (47) | 15 (18)
Difference, % from Vehicle (95% CI) | 18 (5, 31) |  | 26 (17, 34) |  | 29 (15, 42)

† IGA success is defined as an IGA score of 0 or 1 and with ≥ 2-grade improvement from baseline.
‡ Trial 1 enrolled subjects from the United States, Australia, and Poland.
Subjects with missing IGA scores were imputed as failures.

16 HOW SUPPLIED/STORAGE AND HANDLING

How supplied
ADQUEY (difamilast) ointment, 1% is a white to off-white ointment supplied in the following packages:

- 27 g tube (NDC 72893-017-08)
- 85 g tube (NDC 72893-017-09)

Storage and Handling

Store at 20°C–25°C (68°F–77°F); excursions permitted to 15°C–30°C (59°F–86°F). [see USP Controlled Room Temperature].
Store away from direct sunlight, heat, and moisture.
Keep tube tightly closed.

17 PATIENT COUNSELING INFORMATION

Advise patients or caregivers to read the FDA-approved patient labeling (Patient Information).
Administration
Advise patients or caregivers that ADQUEY is for topical use only and is not for ophthalmic, oral, or intravaginal use [see Dosage and Administration (2)].
Lactation
Advise breastfeeding women not to apply ADQUEY directly to the nipple or areola to minimize potential infant exposure. Instruct patients to avoid inadvertent contact of treated areas with the infant’s skin [see Use in Specific Populations (8.2)].

(Made in Canada)

Manufactured for:
Acrotech Biopharma Inc
East Windsor, NJ 08520 USA

PATIENT INFORMATION
ADQUEYTM (ahd kway)
(difamilast)
ointment, for topical use

Important information: ADQUEY is for use on the skin (topical use) only. Do not use ADQUEY near or in your eyes, mouth, or vagina.

What is ADQUEY?
ADQUEY is a prescription medicine used on the skin (topical) to treat adults and children 2 years of age and older with mild to moderate atopic dermatitis.
It is not known if ADQUEY is safe and effective in children younger than 2 years of age.

Before using ADQUEY, tell your healthcare provider about all your medical conditions,
including if you:

- are pregnant or plan to become pregnant. It is not known if ADQUEY will harm your unborn baby.
- are breastfeeding or plan to breastfeed. It is not known if ADQUEY passes into your breast milk or if it may harm your baby. Talk to your healthcare provider about the best way to feed your baby during treatment with ADQUEY.
  Breastfeeding women using ADQUEY should not apply ADQUEY directly to the nipple or areola to avoid contact with your baby. Avoid contact between your baby and any skin areas treated with ADQUEY.

Tell your healthcare provider about all the medicines you take, including prescription and over-the-counter medicines, vitamins, and herbal supplements.

How should I use ADQUEY?

- Use ADQUEY exactly as your healthcare provider tells you to use it.
- Apply a thin layer of ADQUEY to the affected areas 2 times a day. Rub the ointment in completely until you no longer see it on your skin.
- Avoid applying ADQUEY to areas of the skin that are red, warm, swollen or painful.
- Wash your hands after applying ADQUEY. If someone else applies ADQUEY for you, they should wash their hands after applying it.

What are the possible side effects of ADQUEY?
The most common side effects of ADQUEY include: pain or swelling in the nose and throat (nasopharyngitis).
These are not all of the possible side effects of ADQUEY.
Call your doctor for medical advice about side effects. You may report side effects to FDA at 1-800-FDA-1088.

How should I store ADQUEY?

- Store ADQUEY at room temperature between 68°F to 77°F (20°C to 25°C).
- Store ADQUEY away from direct sunlight, heat and moisture.
- Keep ADQUEY tube tightly closed after each use.

Keep ADQUEY and all medicines out of the reach of children.

General information about the safe and effective use of ADQUEY.
Medicines are sometimes prescribed for purposes other than those listed in a Patient Information leaflet. Do not use ADQUEY for a condition for which it was not prescribed. Do not give ADQUEY to other people, even if they have the same symptoms that you have. It may harm them. You can ask your pharmacist or healthcare provider for information about ADQUEY that is written for health professionals.

What are the ingredients in ADQUEY?
Active ingredient: difamilast
Inactive ingredients: mineral oil, paraffin, propylene carbonate, white petrolatum, and white wax.
(Made in Canada)
Manufactured for:Acrotech Biopharma Inc, East Windsor, NJ 08520 USA
For more information, call 1-888-292-9617 or go to www.ADQUEY.com.

This Patient Information has been approved by the U.S. Food and Drug Administration.
Issued: 02/2026